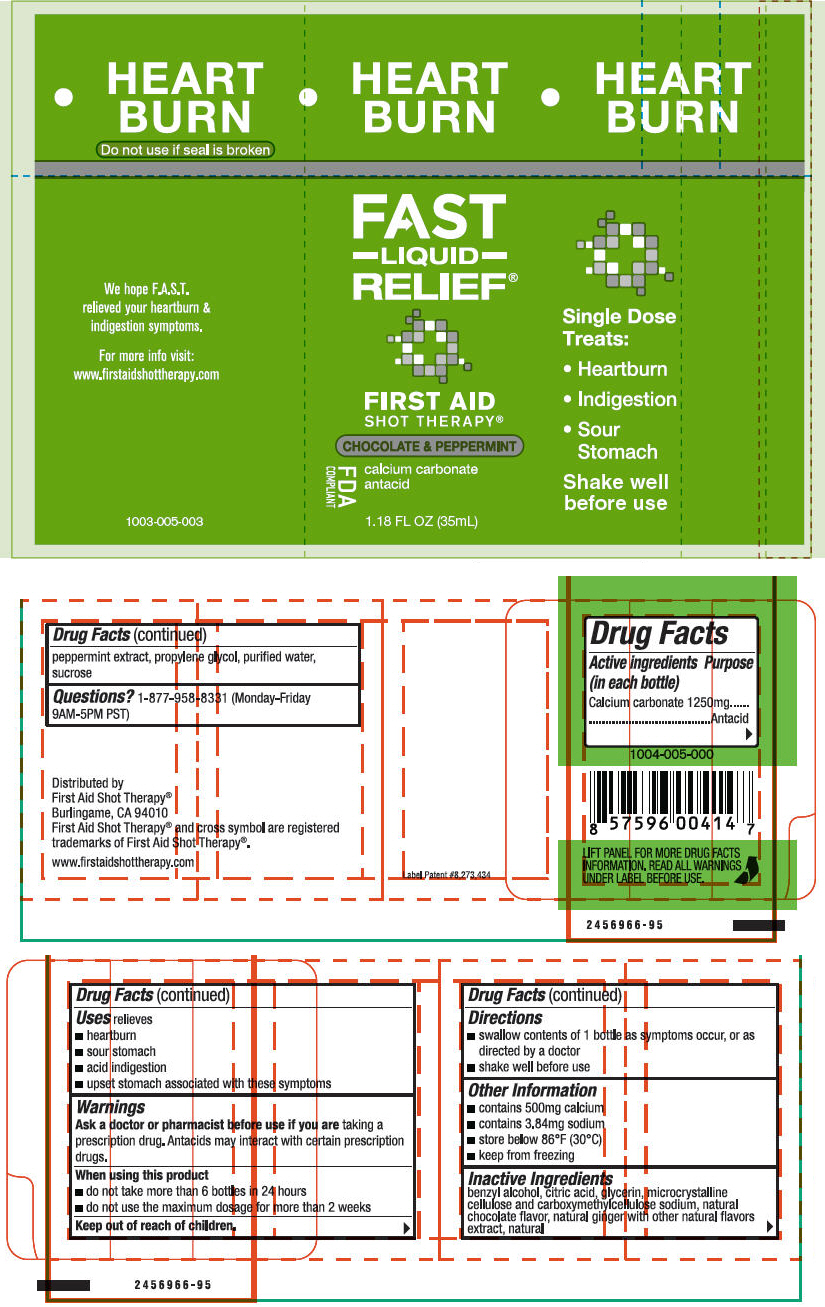 DRUG LABEL: First Aid Shot Therapy Heartburn Relief
NDC: 57815-051 | Form: LIQUID
Manufacturer: First Aid Beverages, Inc.
Category: otc | Type: HUMAN OTC DRUG LABEL
Date: 20150123

ACTIVE INGREDIENTS: Calcium Carbonate 1250 mg/40 mL
INACTIVE INGREDIENTS: Anhydrous Citric Acid; Benzyl Alcohol; Cellulose, Microcrystalline; Glycerin; Propylene Glycol; Sucrose; Water

First Aid Shot Therapy® Heartburn Relief

Drug Facts

Active ingredients

Calcium carbonate 1250mg

Purposes (in each bottle)

Antacid

Uses

relieves

- Heartburn
- Sour stomach
- Acid indigestion
- Upset stomach associated with these symptoms

Warnings

Ask a doctor or pharmacist before use if you are taking a prescription drug. Antacids may interact with certain prescription drugs.

When using this product

- Do not take more than 6 bottles in 24 hours
- Do not use the maximum dosage for more than 2 weeks

Keep out of reach of children. In case of overdose, get medical help or contact a Poison Control Center right away.

Directions

- swallow the contents of 1 bottle as symptoms occur, or as directed by a doctor
- shake well before use

Other Information

- contains 500mg calcium
- contains 3.84mg sodium
- store below 86°F (30°C)
- Keep from freezing

Inactive Ingredients

Benzyl alcohol, citric acid, glycerin, microcrystalline cellulose and caboxymethylcellulose sodium, natural chocolate flavor, natural ginger with other natural flavors, natural peppermint extract, propylene glycol, purified water, sucrose

Questions or comments?

1-877-958-8331 (Monday-Friday 9AM-5PM PST)

Distributed by
First Aid Shot Therapy®
Burlingame, CA 94010

PRINCIPAL DISPLAY PANEL - 35 mL Bottle Label

●
HEART
BURN

FAST
– LIQUID –
RELIEF®

FIRST AID
SHOT THERAPY®

CHOCOLATE & PEPPERMINT

FDA
COMPLIANT

calcium carbonate
antacid

1.18 FL OZ (35mL)